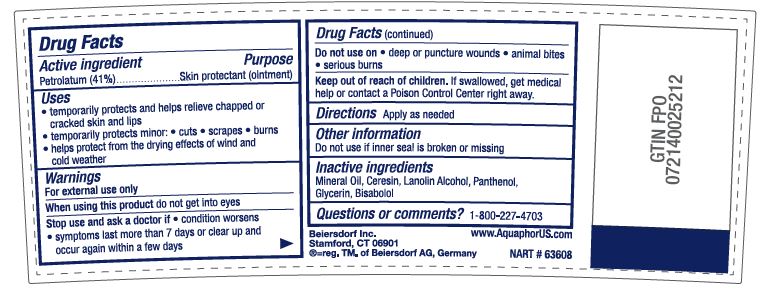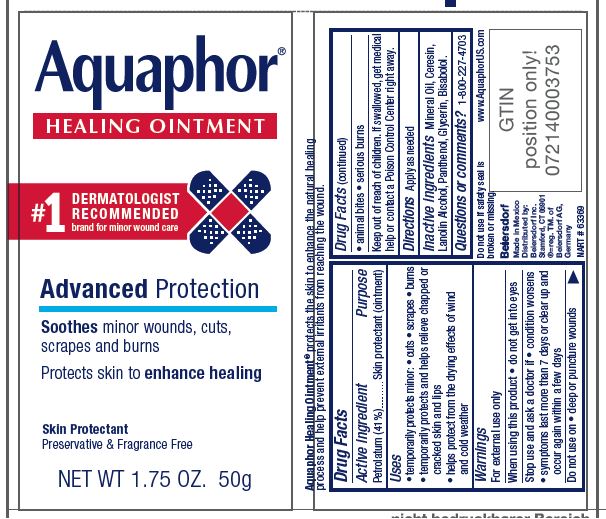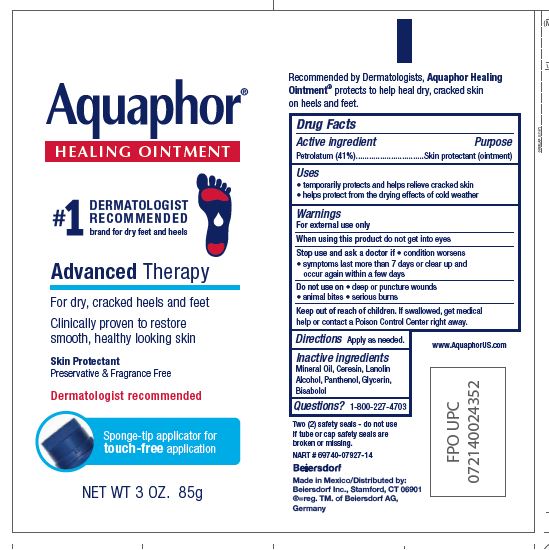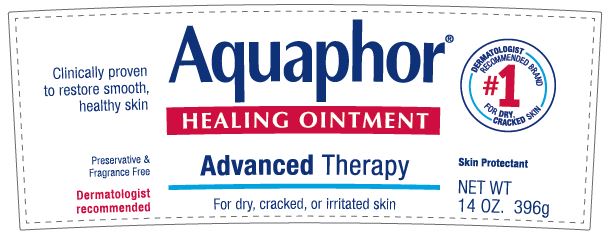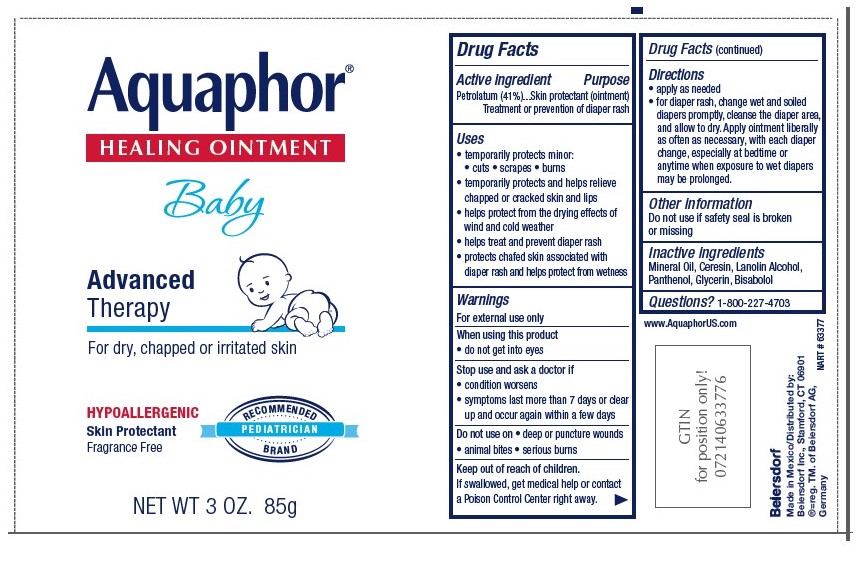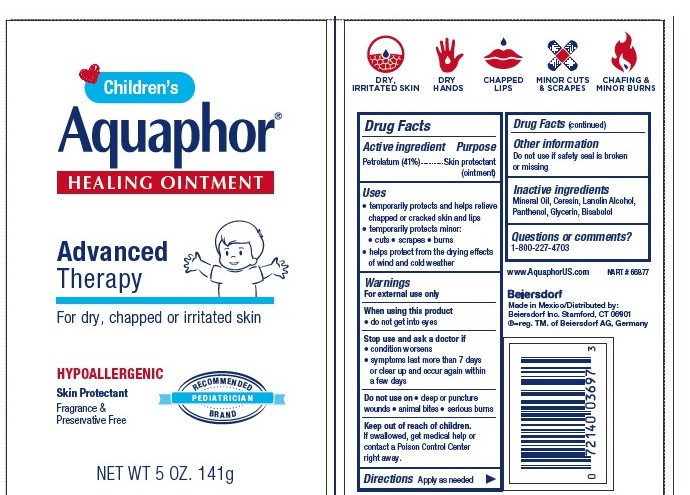 DRUG LABEL: Aquaphor Healing
NDC: 10356-101 | Form: OINTMENT
Manufacturer: Beiersdorf Inc
Category: otc | Type: HUMAN OTC DRUG LABEL
Date: 20251215

ACTIVE INGREDIENTS: PETROLATUM 41 g/100 g
INACTIVE INGREDIENTS: LANOLIN ALCOHOLS; CERESIN; GLYCERIN; PANTHENOL; LEVOMENOL; MINERAL OIL

Aquaphor Healing

ACTIVE INGREDIENT

Petrolatum 41%

PURPOSE

Skin Protectant Ointment

Treatment or Prevention of Diaper Rash

Uses

• temporarily protects minor: • cuts • scrapes • burns
• temporarily protects and helps relieve chapped or cracked skin and lips
• helps protect from the drying effects of wind and cold weather

• helps treat and prevent diaper rash
• protects chafed skin associated with diaper rash and helps protect from wetness

When using this product • do not get into eyes

Do not use on

• deep or puncture wounds • animal bites
• serious burns

Stop use and ask a doctor if • condition worsens
• symptoms last more than 7 days or clear up and occur
again within a few days

Keep out of reach of children. If swallowed, get medical help
or contact a Poison Control Center right away.

INACTIVE INGREDIENT

Mineral Oil, Ceresin, Lanolin Alcohol,
Panthenol, Glycerin, Bisabolol

Questions or comments?
1-800-227-4703

Directions

• apply as needed

• for diaper rash, change wet and soiled diapers promptly, cleanse the diaper area, and allow to dry. Apply ointment liberally as often as necessary, with each diaper change, especially at bedtime or anytime when exposure to wet diapers may be prolonged.

PACKAGE LABEL

Aquaphor Healing Ointment

Number 1 Dermatologist Recommended brand for dry feet and heels

Advanced Therapy
For dry, cracked heels and feet

Clinically proven to restore smooth, healthy looking skin
Skin Protectant
Preservative & Fragrance Free

Dermatolgist recommended

Sponge-tip applicator for touch-free application

Recommended by Dermatolgists, Aquaphor Healing Ointment protects to help heal dry, cracked skin on heels ad feet

Aquaphor Healing Ointment

Advanced Therapy

For dry, cracked or irritated skin

Clinically proven to restore smooth, healthy skin

Preservative and Fragrance Free

Dermatologist recommended

Skin Protectant

Number 1 Dermatologist Recommended brand for dry, cracked skin

Aquaphor Healing Ointment

Baby

Advanced Therapy

For dry, chapped or irritated skin

Hypoallergenic

Skin Protectant

Fragrance Free
Pediatrician recommended brand

Aquaphor Healing Ointment

Number 1 Dermatologist Recommended brand for minor wound care

Advanced Protection

Soothes minor wouds, cuts, scrapes and burns

Protects skin to enhance healing

Skin Protectant

Preservative and Fragrance Free

Aquaphor Healing Ointment protects the skin to enhance the natural healing process

and help prevent external irritants from reaching the wound

Children's

Aquaphor Healing Ointment

Advanced Therapy

For dry, chapped or irritated skin

Hypoallergenic

Skin Protectant

Fragrance and Preservative Free

Pediatrician recommended bran